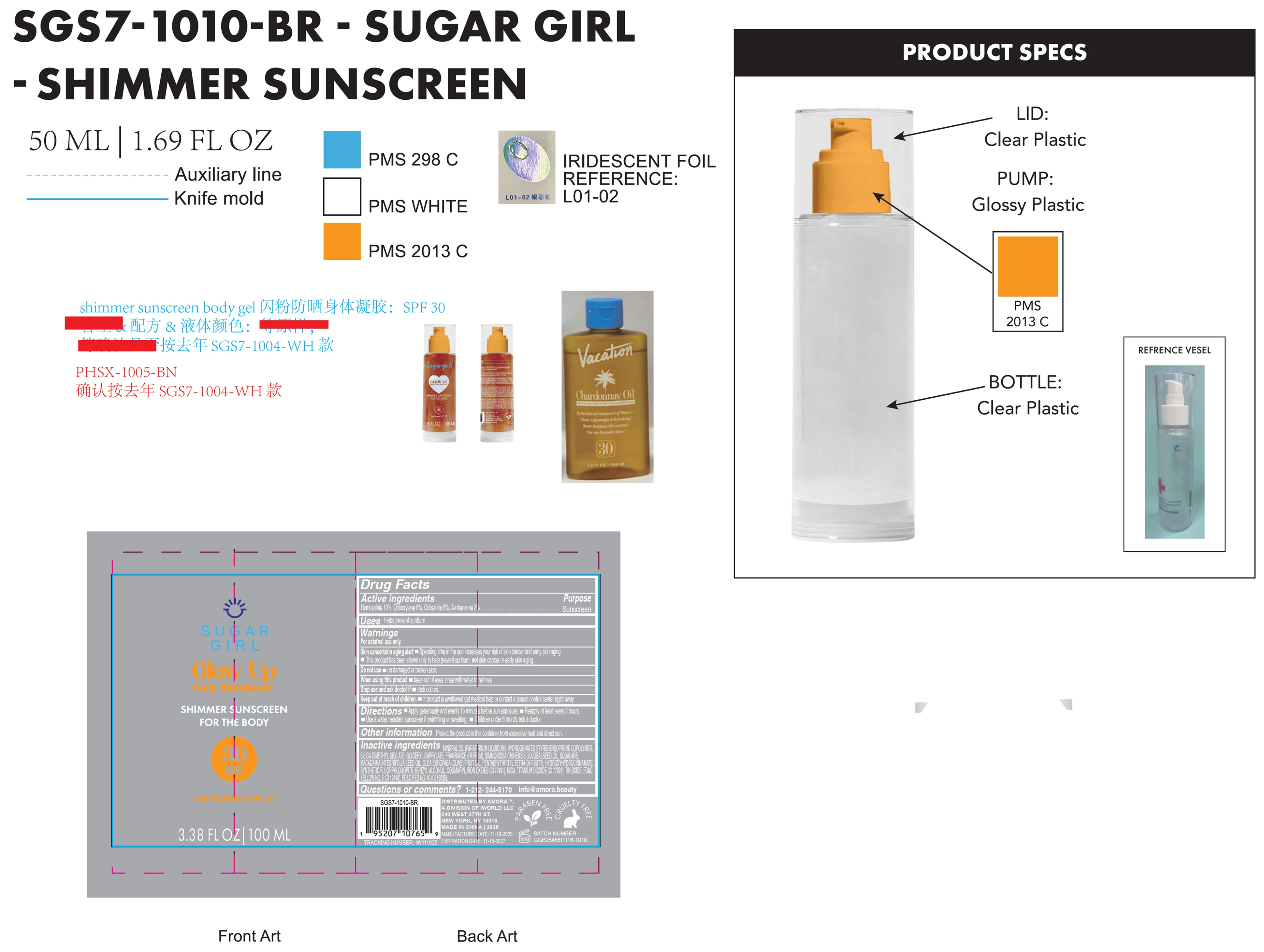 DRUG LABEL: Sugargirl Glow Up Body Illuminator Shimmer Sunscreen SPF 30
NDC: 85179-002 | Form: GEL
Manufacturer: I World LLC
Category: otc | Type: HUMAN OTC DRUG LABEL
Date: 20260210

ACTIVE INGREDIENTS: HOMOSALATE 100 mg/1 mL; OCTOCRYLENE 60 mg/1 mL; OCTISALATE 50 mg/1 mL; AVOBENZONE 30 mg/1 mL
INACTIVE INGREDIENTS: MINERAL OIL; SILICA DIMETHYL SILYLATE; GLYCERYL MONOCAPRYLATE; JOJOBA OIL; SQUALANE; MACADAMIA OIL; OLIVE OIL; PENTAERYTHRITOL TETRAKIS(3-(3,5-DI-TERT-BUTYL-4-HYDROXYPHENYL)PROPIONATE); BENZYL ALCOHOL; COUMARIN; FERRIC OXIDE RED; MICA; TITANIUM DIOXIDE; STANNIC OXIDE; FD&C YELLOW NO. 5; FD&C RED NO. 40

Sugargirl Glow Up Body Illuminator Shimmer Sunscreen SPF 30

Active ingredients

Homosalate 10%, Octocrylene 6%, Octisalate 5%, Avobenzone 3%

Purpose

Sunscreen

Uses

Helps prevent sunburn.

Warnings

For external use only.

Skin cancer/skin aging alert • Spending time in the sun increases your risk of skin cancer and early skin aging.

• This product has been shown only to help prevent sunburn, not skin cancer or early skin aging.

Do not use

- on damaged or broken skin.

When using this product

- Keep out of eyes. rinse with water to remove.

Stop use and ask doctor if

- rash occurs.

Keep out of reach of children.

- If product is swallowed, get medical help or contact a Poison Control Center right away.

Directions

- Apply generously and evenly 15 minutes before sun exposure.
- Reapply at least every 2 hours.
- Use a water resistant sunscreen if swimming or sweating.
- Children under 6 month: ask a doctor.

Other information

Protect the product in this container from excessive heat and direct sun.

Inactive ingredients

MINERAL OIL (PARAFFINUM LIQUIDUM), HYDROGENATED STYRENE/ISOPRENE COPOLYMER, SILICA DIMETHYL SILYLATE, GLYCERYL CAPRYLATE, FRAGRANCE (PARFUM), SIMMONDSIA CHINENSIS (JOJOBA) SEED OIL, SQUALANE, MACADAMIA INTEGRIFOLIA SEED OIL, OLEA EUROPAEA (OLIVE) FRUIT OIL, PENTAERYTHRITYL TETRA-DI-T-BUTYL HYDROXYHYDROCINNAMATE, SYNTHETIC FLUORPHLOGOPITE, BENZYL ALCOHOL, COUMARIN, IRON OXIDES (CI 77491), MICA, TITANIUM DIOXIDE (CI 77891), TIN OXIDE, FD&C YELLOW NO. 5 (CI 19140), FD&C RED NO. 40 (CI 16035).

Questions or comments?

1-212-244-5170